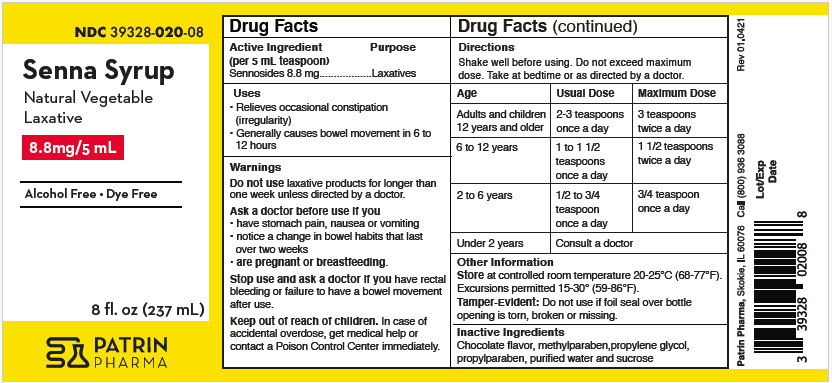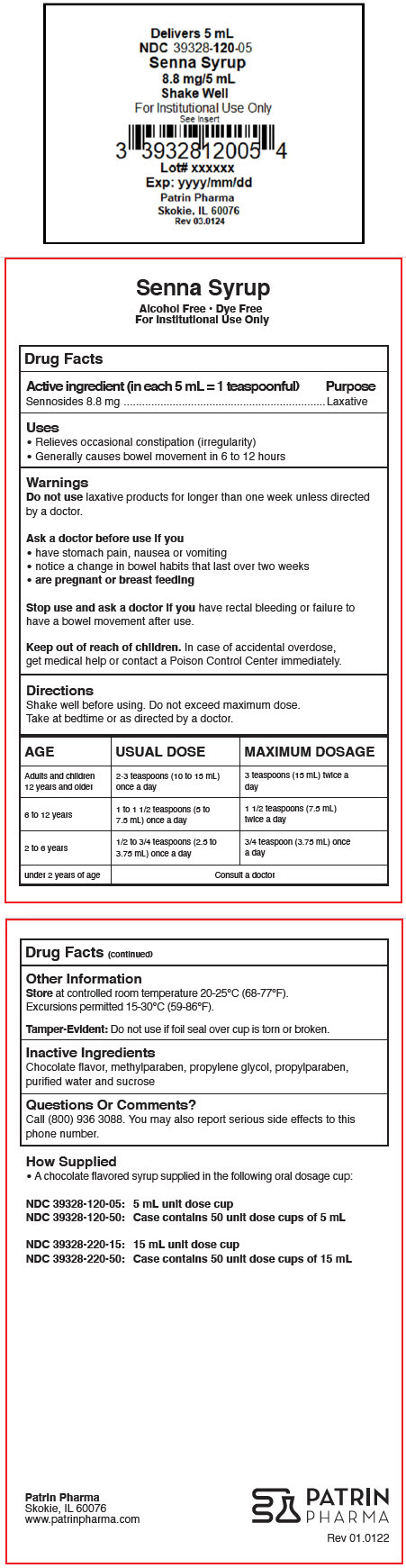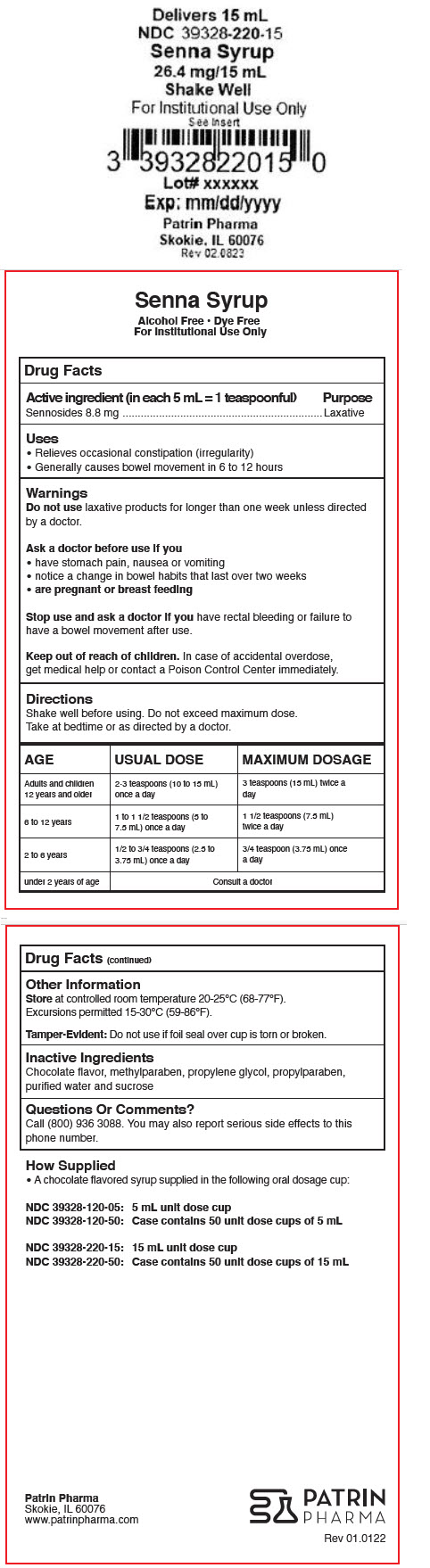 DRUG LABEL: Senna
NDC: 39328-020 | Form: SYRUP
Manufacturer: Patrin Pharma, Inc.
Category: otc | Type: HUMAN OTC DRUG LABEL
Date: 20240530

ACTIVE INGREDIENTS: Sennosides 8.8 mg/5 mL
INACTIVE INGREDIENTS: methylparaben; propylene glycol; propylparaben; water; sucrose

Senna Syrup

Drug Facts

Active ingredient (in each 5 mL = 1 teaspoonful)

Sennosides 8.8 mg

Purpose

Laxative

Uses

- Relieves occasional constipation (irregularity)
- Generally causes bowel movement in 6 to 12 hours

Warnings

Do not use laxative products for longer than one week unless directed by a doctor.

Ask a doctor before use if you

- have stomach pain, nausea or vomiting
- notice a change in bowel habits that last over two weeks
- are pregnant or breast feeding

Stop use and ask a doctor if you have rectal bleeding or failure to have a bowel movement after use.

Keep out of reach of children. In case of accidental overdose, get medical help or contact a Poison Control Center immediately.

Directions

Shake well before using. Do not exceed maximum dose.

Take at bedtime or as directed by a doctor.

AGE | USUAL DOSE | MAXIMUM DOSAGE
Adults and children 12 years and older | 2-3 teaspoons (10 to 15 mL) once a day | 3 teaspoons (15 mL) twice a day
6 to 12 years | 1 to 1 1/2 teaspoons (5 to 7.5 mL) once a day | 1 1/2 teaspoons (7.5 mL) twice a day
2 to 6 years | 1/2 to 3/4 teaspoons (2.5 to 3.75 mL) once a day | 3/4 teaspoon (3.75 mL) once a day
under 2 years of age | Consult a doctor

Other Information

Store at controlled room temperature 20-25°C (68-77°F).

Excursions permitted 15-30°C (59-86°F).

Tamper-Evident: Do not use if foil seal over cup is torn or broken.

Inactive Ingredients

Chocolate flavor, methylparaben, propylene glycol, propylparaben, purified water and sucrose

Questions Or Comments?

Call (800) 936 3088. You may also report serious side effects to this phone number.

How Supplied

- A chocolate flavored syrup supplied in the following oral dosage cup:

NDC 39328-120-05: NDC 39328-120-50: | 5 mL unit dose cup Case contains 50 unit dose cups of 5 mL
NDC 39328-220-15: NDC 39328-220-50: | 15 mL unit dose cup Case contains 50 unit dose cups of 15 mL

Patrin Pharma
Skokie, IL 60076
www.patrinpharma.com

Rev 01.0122

PRINCIPAL DISPLAY PANEL - 237 mL Bottle Label

NDC 39328-020-08

Senna Syrup
Natural Vegetable
Laxative

8.8mg/5 mL

Alcohol Free • Dye Free

8 fl. oz (237 mL)

PATRIN
PHARMA

PRINCIPAL DISPLAY PANEL - 5 mL Cup Label

Delivers 5 mL

NDC 39328-120-05

Senna Syrup

8.8 mg/5 mL

Shake Well

For Institutional Use Only

See Insert

Lot# xxxxxx

Exp: yyyy/mm/dd

Patrin Pharma

Skokie, IL 60076

Rev 03.0124

PRINCIPAL DISPLAY PANEL - 15 mL Cup Label

Delivers 15 mL

NDC 39328-220-15

Senna Syrup

26.4 mg/15 mL

Shake Well

For Institutional Use Only

See Insert

Lot# xxxxxx

Exp: mm/dd/yyyy

Patrin Pharma

Skokie, IL 60076

Rev 02.0823